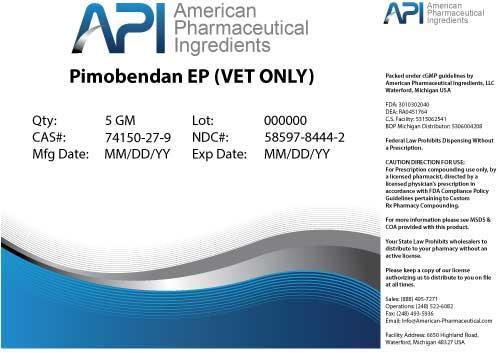 DRUG LABEL: Pimobendan
NDC: 58597-8444 | Form: POWDER
Manufacturer: AMERICAN PHARMACEUTICAL INGREDIENTS LLC
Category: other | Type: BULK INGREDIENT
Date: 20140428

ACTIVE INGREDIENTS: Pimobendan 1 g/1 g

Pimobendan